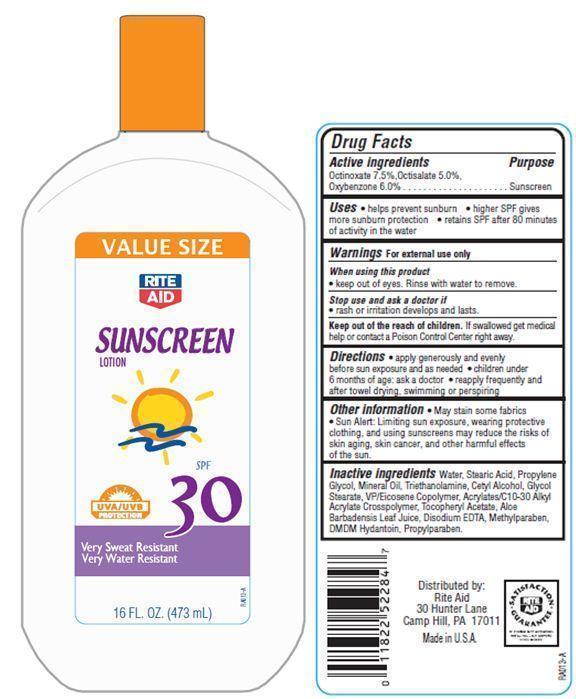 DRUG LABEL: Rite Aid Sunscreen
                
NDC: 11822-9014 | Form: LOTION
Manufacturer: RITE AID CORPORATION
Category: otc | Type: HUMAN OTC DRUG LABEL
Date: 20121205

ACTIVE INGREDIENTS: OCTINOXATE 7.5 g/100 g; OCTISALATE 5 g/100 g; OXYBENZONE 6 g/100 g
INACTIVE INGREDIENTS: WATER; STEARIC ACID; PROPYLENE GLYCOL; MINERAL OIL; TROLAMINE; CETYL ALCOHOL; GLYCOL STEARATE; .ALPHA.-TOCOPHEROL ACETATE; ALOE VERA LEAF; EDETATE DISODIUM; METHYLPARABEN; DMDM HYDANTOIN; PROPYLPARABEN

Drug Facts

Active Ingredients

Octinoxate 7.5%
Octisalate 5.0%
Oxybenzone 6.0%

Purpose

Sunscreen

Uses

- helps prevent sunburn
- higher SPF gives more sunburn protection
- retains SPF after 80 minutes of activity in the water

Warnings

For external use only

When using this product

- keep out of eyes.Rinse with water to remove.

Stop use and ask a doctor if

rash or irritation develops and lasts.

Keep out of the reach of children.

If swallowed get medical help or contact a Poison Control Center right away.

Directions

- apply generously and evenly before sun exposure and as needed
- Children under 6 months of age:ask a doctor
- reapply after towel drying, swimming or perspiring

Other information

- May stain some fabrics
- Sun Alert: Limiting sun exposure, wearing protective clothing, and using sunscreens may reduce the risks of skin aging, skin cancer, and other harmful effects of the sun.

Inactive Ingredients

Water, Stearic Acid, Propylene Glycol, Mineral Oil, Triethanolamine, Cetyl Alcohol, Glycol Stearate, VP/Eicosene Copolymer, Acrylates/C10-30 Alkyl Acrylate Crosspolymer, Tocopheryl Acetate, Aloe Barbadensis Leaf Juice, Disodium EDTA, Methylparaben, DMDM Hydantoin, Propylparaben.

Principal Display Panel

VALUE SIZE
RITE AID
SUNSCREEN LOTION
SPF 30
UVA/UVB PROTECTION
Very Sweat Resistant
Very Water Resistant
16 FL OZ(473 mL)